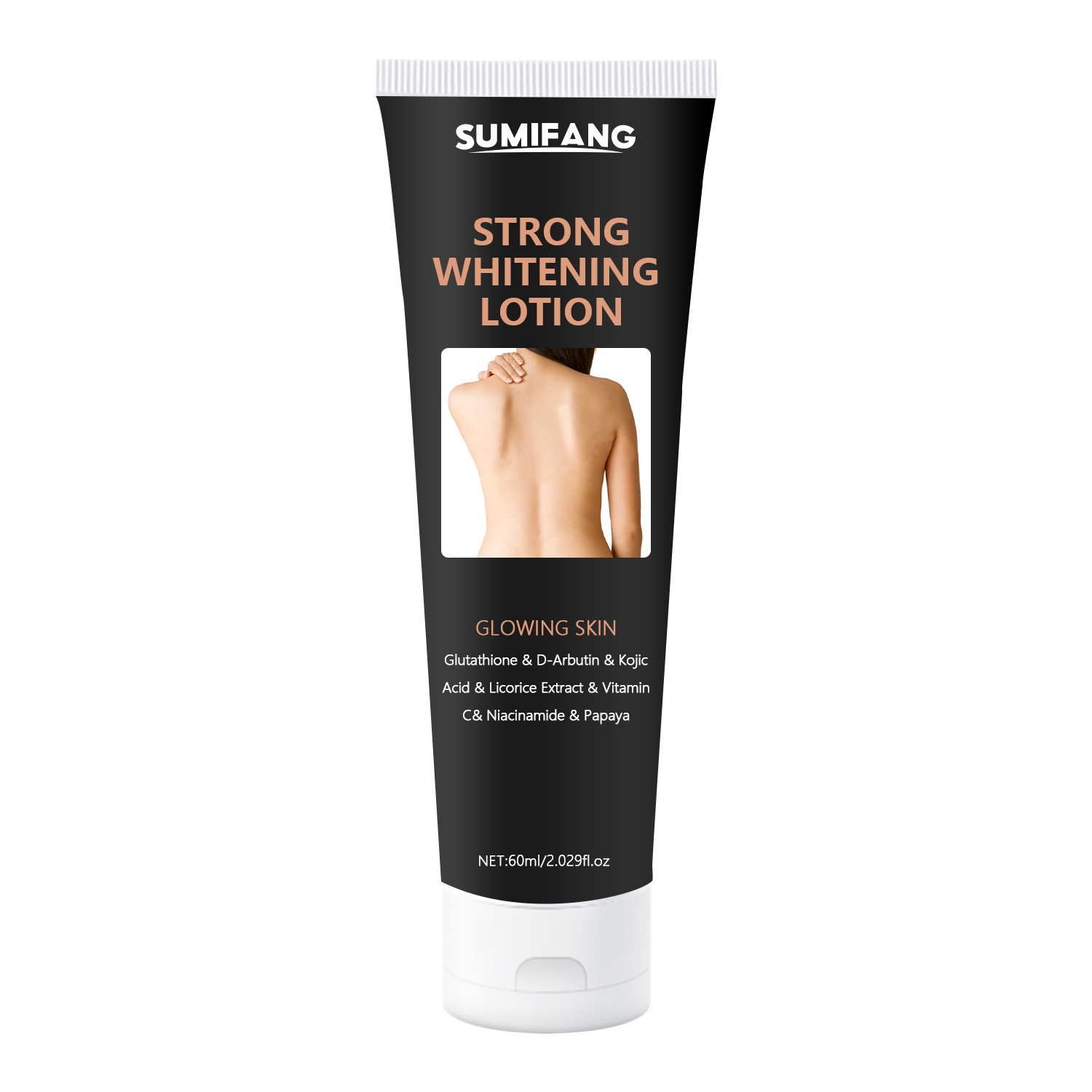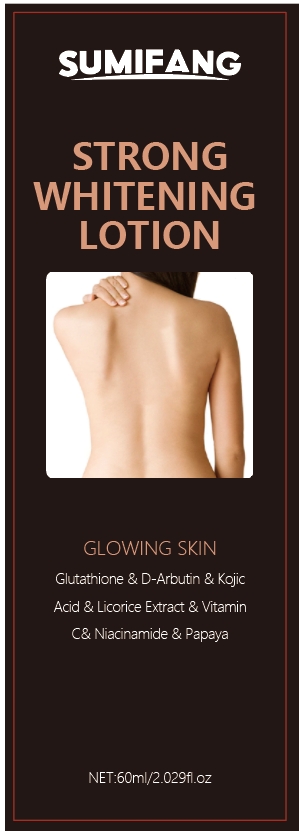 DRUG LABEL: BodyLotion
NDC: 84025-134 | Form: LOTION
Manufacturer: Guangzhou Yanxi Biotechnology Co.. Ltd
Category: otc | Type: HUMAN OTC DRUG LABEL
Date: 20240814

ACTIVE INGREDIENTS: CETEARYL OLIVATE 3 mg/60 mL; NIACINAMIDE 5 mg/60 mL
INACTIVE INGREDIENTS: WATER

DOSAGE AND ADMINISTRATION

Used for skin whitening and relieving dull skin on the body

WARNINGS

Keep out of children

INACTIVE INGREDIENT

Aqua

INDICATIONS AND USAGE

For daily skin care

Keep out of children

PURPOSE

Whitens skin and enhances skin radiance